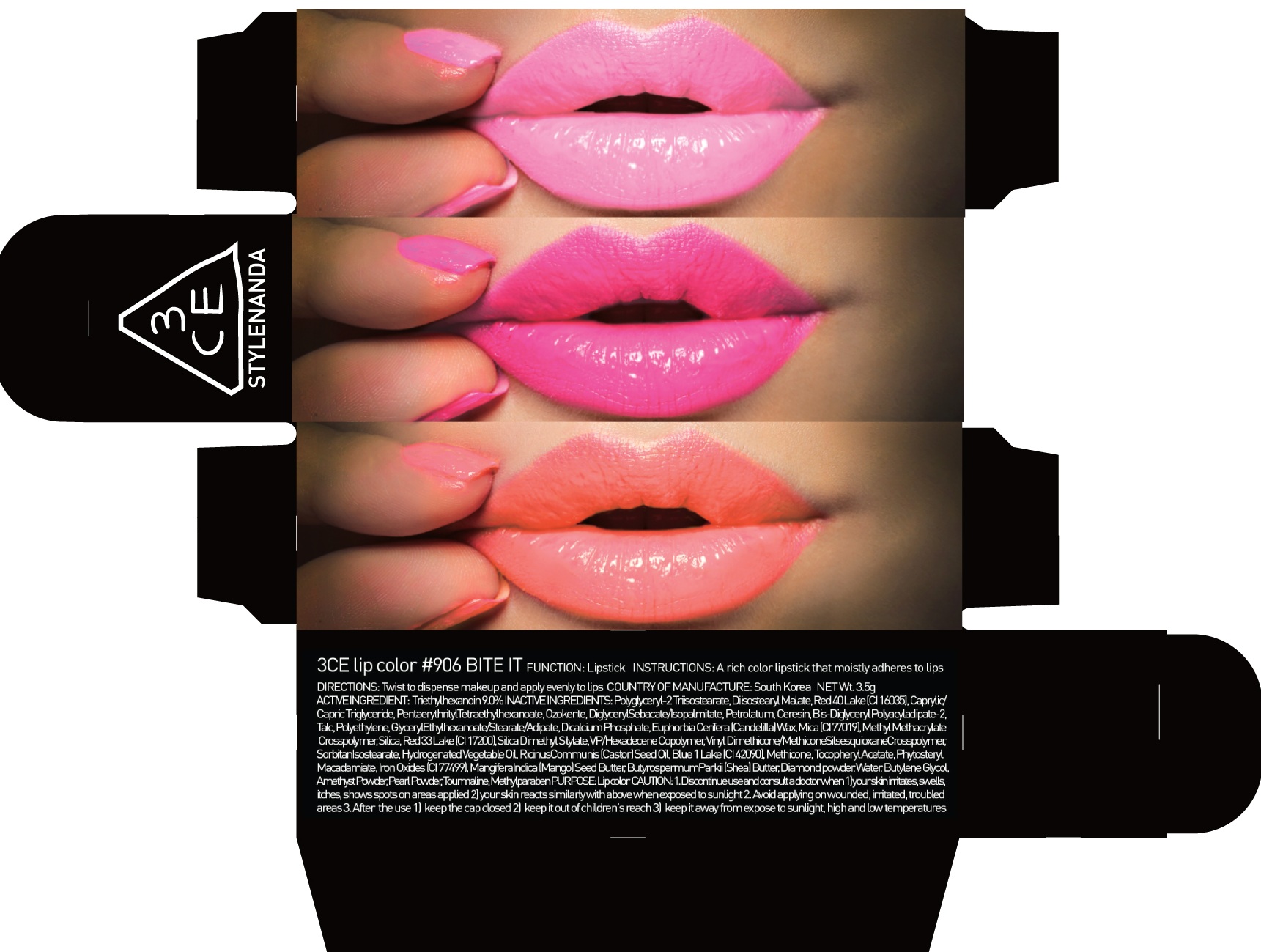 DRUG LABEL: 3CE LIP COLOR 906 BITE IT
NDC: 60764-050 | Form: LIPSTICK
Manufacturer: Nanda Co., Ltd
Category: otc | Type: HUMAN OTC DRUG LABEL
Date: 20160930

ACTIVE INGREDIENTS: Triethylhexanoin 0.31 g/3.5 g
INACTIVE INGREDIENTS: Diisostearyl Malate; Ceresin

ACTIVE INGREDIENT

Active Ingredient: Triethylhexanoin 9.0%

INACTIVE INGREDIENT

Inactive Ingredients: Polyglyceryl-2 Triisostearate, Diisostearyl Malate, Red 40 Lake (CI 16035), Caprylic/Capric Triglyceride, PentaerythritylTetraethylhexanoate, Ozokerite, DiglycerylSebacate/Isopalmitate, Petrolatum, Ceresin, Bis-Diglyceryl Polyacyladipate-2, Talc, Polyethylene, GlycerylEthylhexanoate/Stearate/Adipate, Dicalcium Phosphate, Euphorbia Cerifera (Candelilla) Wax, Mica (CI 77019), Methyl Methacrylate Crosspolymer, Silica, Red 33 Lake (CI 17200), Silica Dimethyl Silylate, VP/Hexadecene Copolymer, Vinyl Dimethicone/MethiconeSilsesquioxaneCrosspolymer, SorbitanIsostearate, Hydrogenated Vegetable Oil, RicinusCommunis (Castor) Seed Oil, Blue 1 Lake (CI 42090), Methicone, Tocopheryl Acetate, PhytosterylMacadamiate, Iron Oxides (CI 77499), MangiferaIndica (Mango) Seed Butter, ButyrospermumParkii (Shea) Butter, Diamond powder, Water, Butylene Glycol, Amethyst Powder, Pearl Powder, Tourmaline, Methylparaben

PURPOSE

Purpose: Lip color

CAUTION

CAUTION: 1. Discontinue use and consult a doctor when - your skin irritates, swells, itches, shows spots on areas applied - your skin reacts similarly with above when exposed to sunlight 2. Avoid applying on wounded, irritated, troubled areas 3. After the use - keep the cap closed - keep it out of children's reach - keep it away from expose to sunlight, high and low temperatures

KEEP OUT OF REACH OF CHILDREN

keep it out of children's reach

INSTRUCTIONS

INSTRUCTIONS: A rich color lipstick that moistly adheres to lips.

Directions

Directions: Twist to dispense makeup and apply evenly to lips